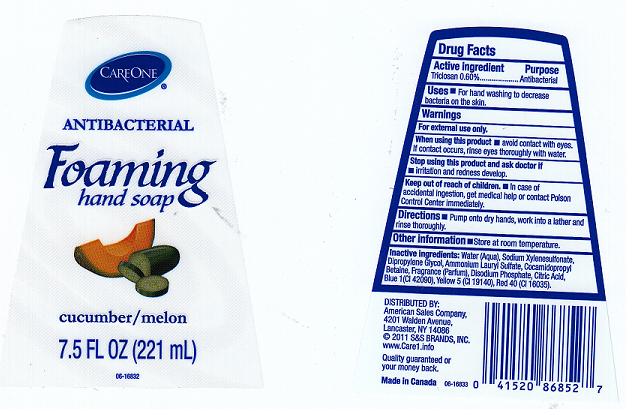 DRUG LABEL: ANTIBACTERIAL FOAMING HAND SP CUCUMBER AND MELON
NDC: 41520-167 | Form: LIQUID
Manufacturer: AMERICAN SALES COMPANY
Category: otc | Type: HUMAN OTC DRUG LABEL
Date: 20110524

ACTIVE INGREDIENTS: TRICLOSAN 0.6 mL/100 mL
INACTIVE INGREDIENTS: WATER; SODIUM XYLENESULFONATE; DIPROPYLENE GLYCOL; AMMONIUM LAURYL SULFATE; COCAMIDOPROPYL BETAINE; SODIUM PHOSPHATE, DIBASIC, DIHYDRATE; CITRIC ACID MONOHYDRATE; FD&C BLUE NO. 1; FD&C YELLOW NO. 5; FD&C RED NO. 40

DRUG FACTS

ACTIVE INGREDIENT

TRICLOSAN 0.60 PERCENT

PURPOSE

ANTIBACTERIAL

USES

FOR HAND WASHING TO REDUCE BACTERIA ON THE SKIN.

WARNINGS

FOR EXTERNAL USE ONLY.

KEEP OUT OF REACH OF CHILDREN

IN CASE OF ACCIDENTAL INGESTION, GET MEDICAL HELP OR CONTACT A POISON CONTROL CENTER IMMEDIATELY.

WHEN USING THIS PRODUCT

AVOID CONTACT WITH EYES.IF CONTACT OCCURS, RINSE EYES THROUGHLY WITH WATER.

STOP USING THIS PRODUCT AND ASK DOCTOR IF

IRRITATION AND REDNESS DEVELOP.

DIRECTIONS

PUMP ONTO DRY HANDS, WORK INTO LATHER AND RINSE THOROUGHLY.

OTHER INFORMATION

STORE AT ROOM TEMPERATURE.

INACTIVE INGREDIENTS

WATER, SODIUM XYLENESULFONATE, DIPROPYLENE GLYCOL,AMMONIUM LAURYL SULFATE, COCAMIDOPROPYL BETAINE, FRAGRANCE, DISODIUM PHOSPHATE, CITRIC ACID, BLUE 1, YELLOW 5, RED 40.